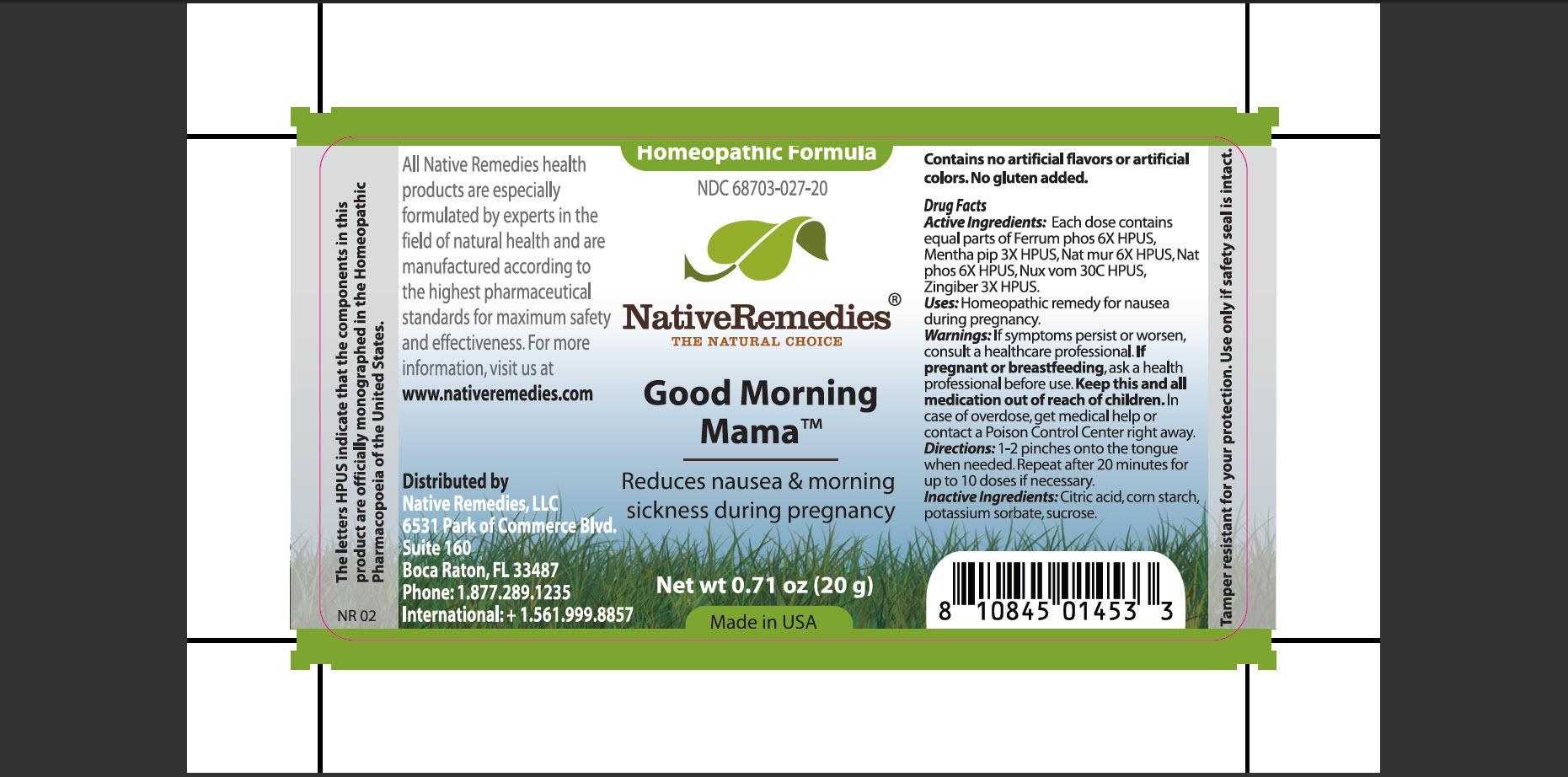 DRUG LABEL: Good Morning Mama
NDC: 68703-027 | Form: GRANULE
Manufacturer: Native Remedies, LLC
Category: homeopathic | Type: HUMAN OTC DRUG LABEL
Date: 20121227

ACTIVE INGREDIENTS: FERROSOFERRIC PHOSPHATE 6 [hp_X]/13.33 mg; MENTHA PIPERITA 3 [hp_X]/13.33 mg; SODIUM CHLORIDE 6 [hp_X]/13.33 mg; SODIUM PHOSPHATE, DIBASIC, HEPTAHYDRATE 6 [hp_X]/13.33 mg; STRYCHNOS NUX-VOMICA SEED 30 [hp_C]/13.33 mg; GINGER 3 [hp_X]/13.33 mg
INACTIVE INGREDIENTS: CITRIC ACID MONOHYDRATE; STARCH, CORN; POTASSIUM SORBATE; SUCROSE

Good Morning Mama

PURPOSE

Reduces nausea and morning sickness during pregnancy

ACTIVE INGREDIENT

Active Ingredients: Each dose contains equal parts of Ferrum phos 6X HPUS, Mentha pip 3X HPUS, Nat mur 6X HPUS, Nat phos 6X HPUS, Nux vom 30C HPUS, Zingiber 3X HPUS

INDICATIONS AND USAGE

Uses: Homeopathic remedy for nausea during pregnancy.

WARNINGS

Warnings: If symptoms persist or worsen, consult a healthcare professional.

PREGNANCY OR BREAST FEEDING

If pregnant or breastfeeding, ask a health professional before use.

KEEP OUT OF REACH OF CHILDREN

Keep this and all medication out of reach of children.

OVERDOSAGE

In case of overdose, get medical help or contact a Poison Control Center right away.

DOSAGE AND ADMINISTRATION

Directions: 1-2 pinches onto tongue when needed. Repeat after 20 minutes for up to 10 doses if necessary.

INACTIVE INGREDIENT

Inactive Ingredients: Citric acid, corn starch, potassium sorbate, sucrose.

PATIENT COUNSELING INFORMATION

The letters HPUS indicate that the components in this product are officially monographed in the Homeopathic Pharmacopoeia of the United States.

All Native Remedies health products are especially formulated by experts in the field of natural health and are manufactured according to the highest pharmaceutical standards for maximum safety and effectiveness. For more information, visit us at www.nativeremedies.com

Distributed by
Native Remedies, LLC
6531 Park of Commerce Blvd.
Siut 160
Boca Raton, Fl 33487
Phone: 1.877.289.1235
International: +1.561.999.8857

STORAGE AND HANDLING

Tamper resistant for your protection. Use only if safety seal is intact.